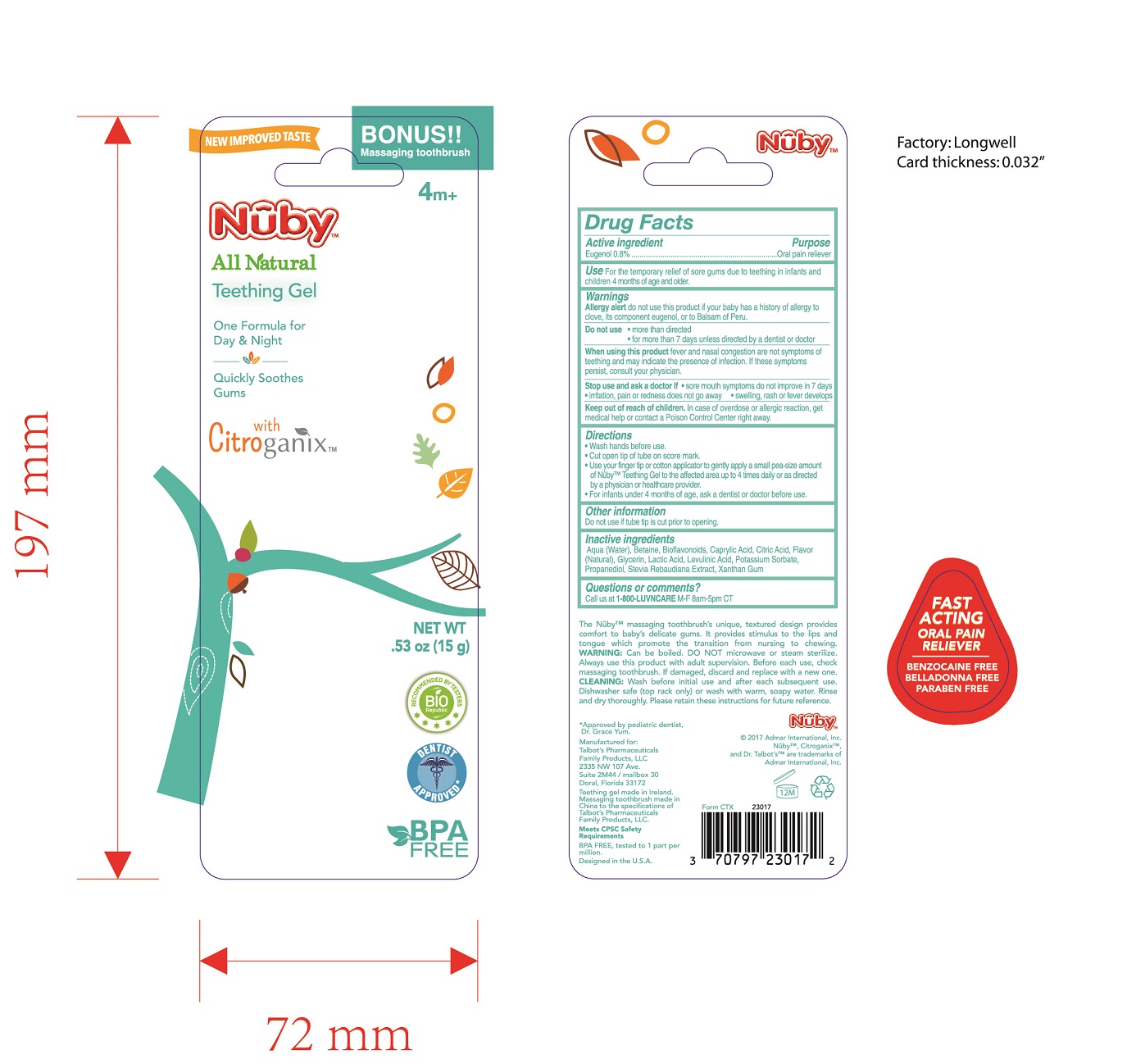 DRUG LABEL: Nuby Teething Gel
NDC: 71552-231 | Form: GEL
Manufacturer: Europharma Concepts limited
Category: otc | Type: HUMAN OTC DRUG LABEL
Date: 20170623

ACTIVE INGREDIENTS: EUGENOL 8 mg/1 g
INACTIVE INGREDIENTS: WATER

Active Ingredient

Eugenol 0.8%

Purpose

Oral pain reliever

Keep out of reach of children

In case of overdose or allergic reaction, get medical help or contact a Poison Control Center right away.

Warnings

Allergy alert do not use this product if your baby has a history of allergy to clove, its component eugenol, or to Balsam of Peru.

Do not use

more than directed

for more than 7 days unless directed by a dentist or doctor

When using this product fever and nasal congestion are not symptoms of teething and may indicate the presence of infection. If these symptoms persist, consult your physician.

Stop use and ask a doctor if

sore mouth symptoms do not improve in 7 days

irritation, pain or redness does not go away

swelling, rash or fever develops

Directions

Wash hands before use.

Cut open tip of tube on score mark.

Use your finger tip or cotton applicator to gently apply a small pea-size amount of Nuby Teething Gel to the affected area up to 4 times daily or as directed by a physician or healthcare provider.

For infants under 4 months of age, ask a dentist or doctor before use.

Inactive Ingredients

Aqua (Water), Betaine, Bioflavonoids, Caprylic Acid, Citric Acid, Flavor (Natural), Glycerin, Lactic Acid, Levulinic Acid, Potassium Sorbate, Propanediol, Stevia Rebaudiana Extract, Xanthan Gum

Use

For the temporary relief of sore gums due to teething in infants and children 4 months of age and older.